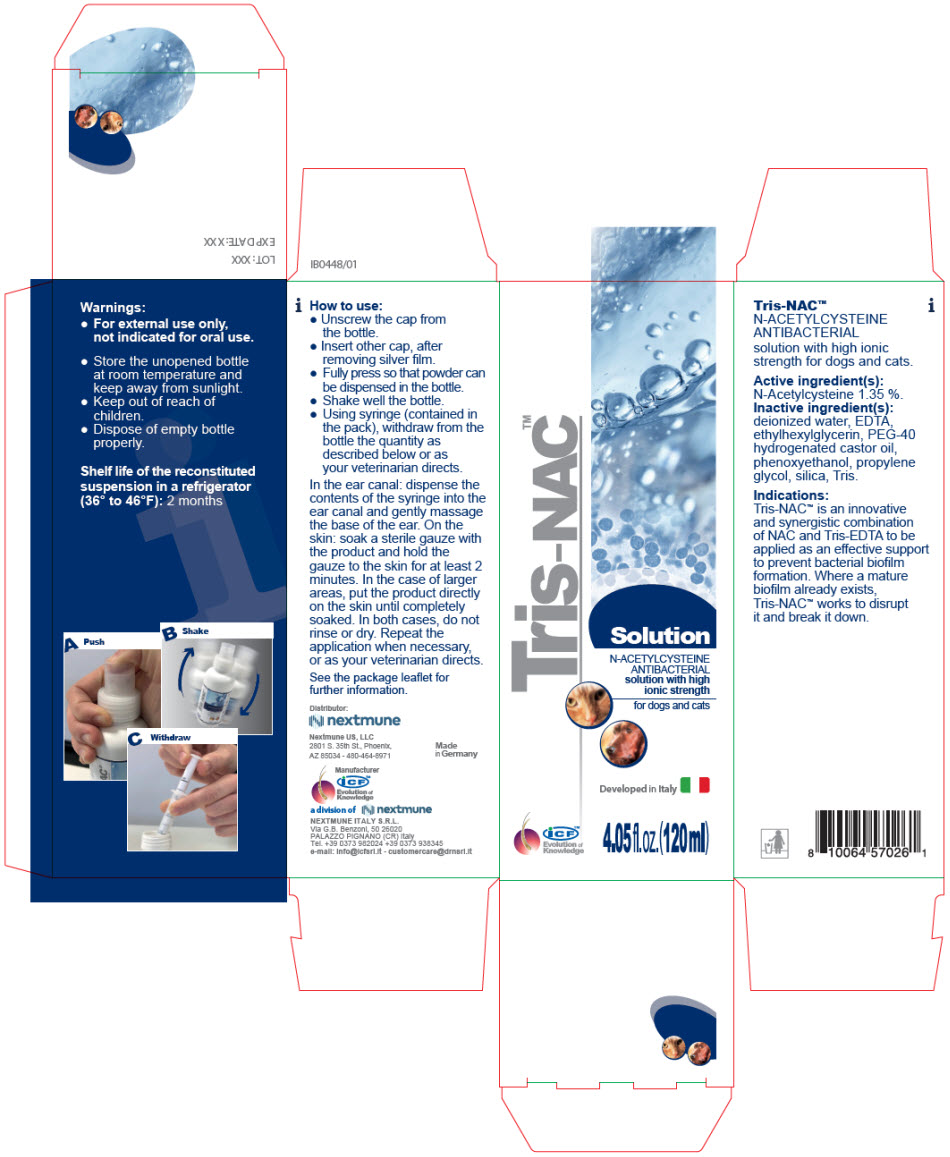 DRUG LABEL: Tris-NAC
NDC: 86127-011 | Form: SOLUTION
Manufacturer: Nextmune AB
Category: animal | Type: OTC ANIMAL DRUG LABEL
Date: 20220513

ACTIVE INGREDIENTS: ACETYLCYSTEINE 1.35 mg/1 mL
INACTIVE INGREDIENTS: EDETIC ACID; WATER; ETHYLHEXYLGLYCERIN; PROPYLENE GLYCOL; PEG-40 CASTOR OIL; SILICON DIOXIDE; PHENOXYETHANOL; TROMETHAMINE

Tris-NAC™

N-ACETYLCYSTEINE ANTIBACTERIAL solution with high ionic strength for dogs and cats.

Active ingredient(s):

N-Acetylcysteine 1.35 %.

Inactive ingredient(s):

deionized water, EDTA, ethylhexylglycerin, PEG-40 hydrogenated castor oil, phenoxyethanol, propylene glycol, silica, Tris.

Indications:

Tris-NAC™ is an innovative and synergistic combination of NAC and Tris-EDTA to be applied as an effective support to prevent bacterial biofilm formation. Where a mature biofilm already exists, Tris-NAC™ works to disrupt it and break it down.

Warnings:

- For external use only, not indicated for oral use.
- Store the unopened bottle at room temperature and keep away from sunlight.
- Keep out of reach of children.
- Dispose of empty bottle properly.

STORAGE AND HANDLING

Shelf life of the reconstituted suspension in a refrigerator (36° to 46°F): 2 months

DOSAGE AND ADMINISTRATION

How to use:

- Unscrew the cap from the bottle.
- Insert other cap, after removing silver film.
- Fully press so that powder can be dispensed in the bottle.
- Shake well the bottle.
- Using syringe (contained in the pack), withdraw from the bottle the quantity as described below or as your veterinarian directs.

In the ear canal: dispense the contents of the syringe into the ear canal and gently massage the base of the ear. On the skin: soak a sterile gauze with the product and hold the gauze to the skin for at least 2 minutes. In the case of larger areas, put the product directly on the skin until completely soaked. In both cases, do not rinse or dry. Repeat the application when necessary, or as your veterinarian directs.

See the package leaflet for further information.

Distributor:
nextmune

Nextmune US, LLC
2801 S. 35th St., Phoenix,
AZ 85034 - 480-464-8971

Made
in Germany

Manufacturer
icf™
Evolution of
Knowledge
a division of nextmune

NEXTMUNE ITALY S.R.L.
Via G.B. Benzoni, 50 26020
PALAZZO PIGNANO (CR) Italy
Tel. +39 0373 982024 +39 0373 938345
e-mail: info@icfsrl.it - customercare@drnsrl.it

PRINCIPAL DISPLAY PANEL - 120 ml Bottle Carton

Tris-NAC™

Solution

N-ACETYLCYSTEINE
ANTIBACTERIAL
solution with high
ionic strength

for dogs and cats

Developed in Italy

icf™
Evolution of
Knowledge

4.05 fl. oz. (120 ml)